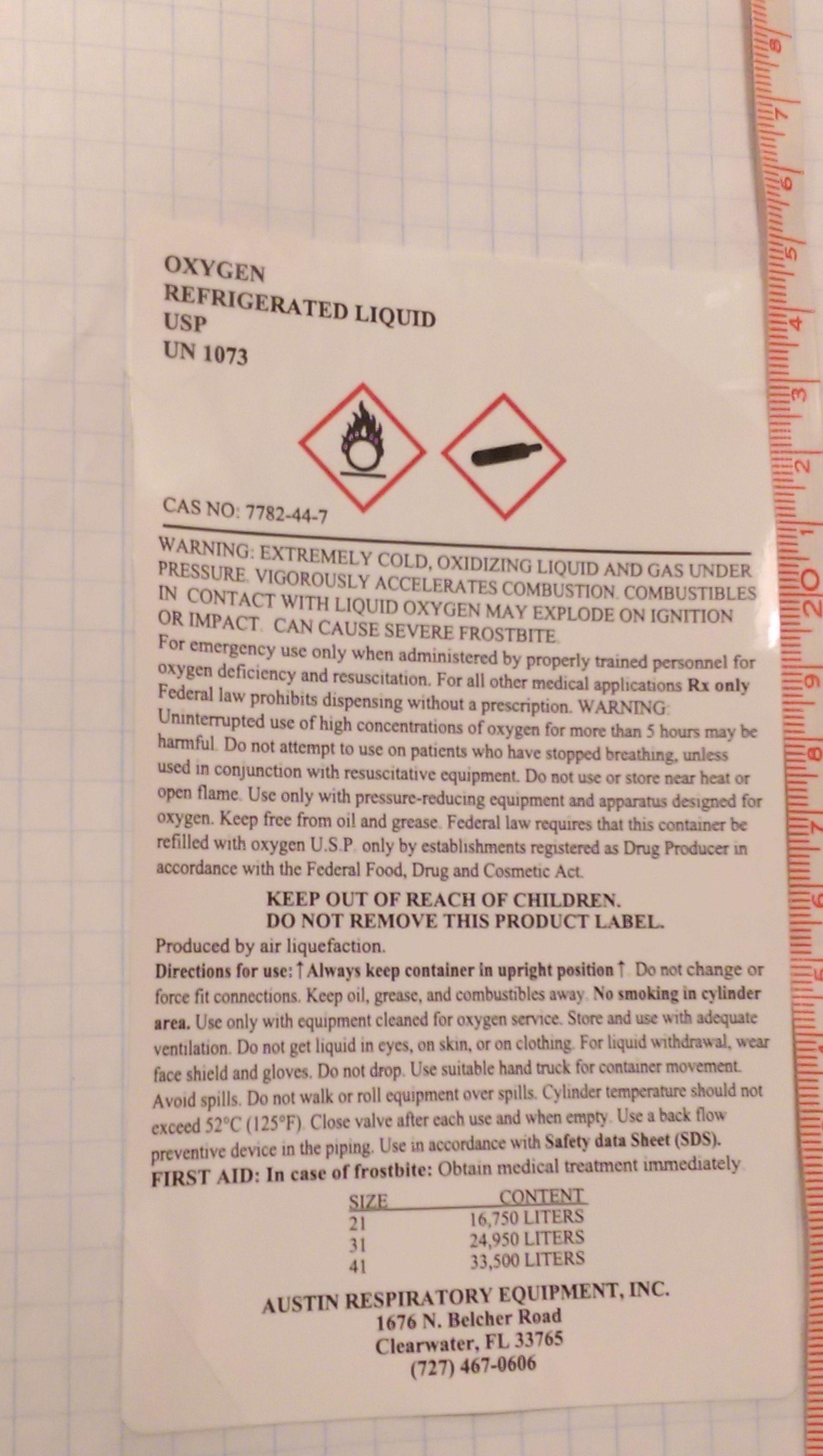 DRUG LABEL: oxygen
NDC: 64540-011 | Form: GAS
Manufacturer: Austin Respiratory Equipment,inc
Category: prescription | Type: HUMAN PRESCRIPTION DRUG LABEL
Date: 20171113

ACTIVE INGREDIENTS: OXYGEN 990 mL/1 L

PACKAGE LABEL

OXYGEN,

REFRIGERATED LIQUID

USP

UN: 1073

CAS NO:7782-44-7

_________________________________________________________________

WARNING

EXTREMELY COLD, OXIDIZING LIQUID AND GAS UNDER PRESSURE.

VIGOROUSLY ACCELERATES COMBUSTION. COMBUSTIBLES IN

CONTACT WITYH LIQUID OXYGEN MAY EXPLODE ON IGNITION OR

IMPACT. CAN CAUSE SEVERE FROSTBITE.

For emergency use only when administered by properly trained personnel for

Oxygen deficiency and resuscitation. For all other medical applications Rx only

Federal law prohibits dispensing without a prescription. WARNING: Uninterrupted

Use of high concentrations of oxygen over a long duration, without monitoring its

Effect on oxygen content of arterial blood, may be harmful. use only with pressure reducing equipment and apparatus designed for oxygen. Do not attempt to use on

Patients who have stopped breathing, unless used in conjunction with resuscitative

equipment. Federal law requires that this Container be Refilled with oxygen U.S.P.

only by Establishments Registered as Drug Producer in accordance with the Federal

Food, Drug and Cosmetic Act.

KEEP OUT OF REACH OF CHILDERN.

DO NOT REMOVE THIS PRODUCT LABEL.

Produced by Air Liquefaction.

Directions for use:↑Always keep container in upright position↑. Do not change or force fit connections. Keep oil, grease, and combustibles away. No smoking in cylinder area. use only with equipment cleaned for oxygen service. Store and use with adequate ventilation. Do not get liquid in eyes, on skin, or on clothing. For liquid withdrawal, wear face shield and gloves. Do not drop. Use suitable hand truck for container movement.

Avoid spills. Do not walk or roll equipment over spills. Cylinder temperature should not exceed 52°C (125°F).Close valve after each use and when empty. Use a back flow preventive device in the piping. Use in accordance with Safety data Sheet. (SDS).

FIRST AID: in case of Frostbite: obtain medical treatment immediately.

SIZE CONTENT

21 16,750 LITERS

31 24,950 LITERS

41 33,500 LITERS

AUSTIN RESPIRATORY EQUIPMENT, INC.

1676 N. Belcher Road

Clearwater, FL. 33765

(727) 467-0606